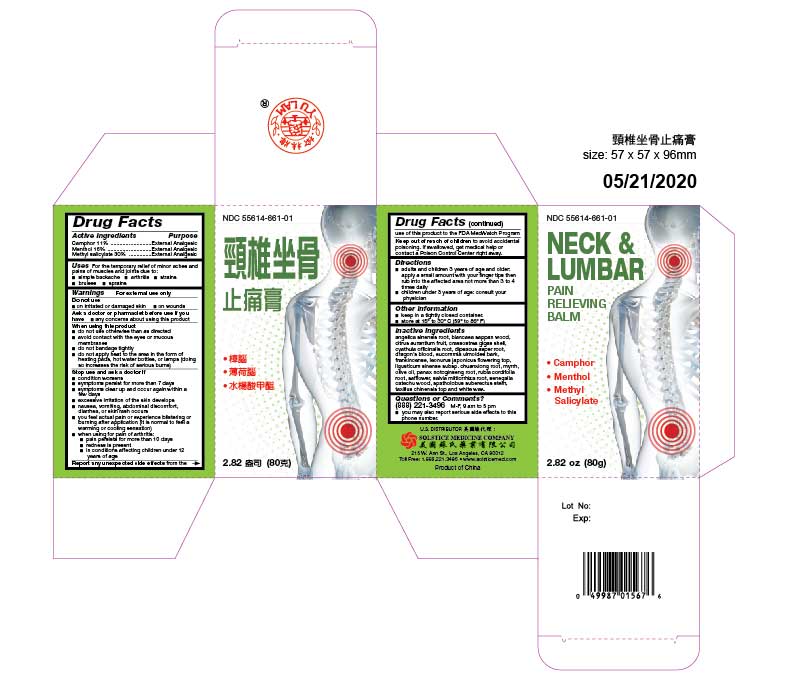 DRUG LABEL: NECK AND LUMBAR PAIN RELIEVING BALM
NDC: 55614-661 | Form: OINTMENT
Manufacturer: MADISON ONE ACME INC
Category: otc | Type: HUMAN OTC DRUG LABEL
Date: 20251110

ACTIVE INGREDIENTS: CAMPHOR (SYNTHETIC) 11 g/100 g; MENTHOL 16 g/100 g; METHYL SALICYLATE 30 g/100 g
INACTIVE INGREDIENTS: ANGELICA SINENSIS ROOT; BIANCAEA SAPPAN WOOD; CITRUS AURANTIUM FRUIT; CRASSOSTREA GIGAS SHELL; CYATHULA OFFICINALIS ROOT; DIPSACUS ASPER ROOT; DRAGON'S BLOOD; EUCOMMIA ULMOIDES BARK; FRANKINCENSE; LEONURUS JAPONICUS FLOWERING TOP; LIGUSTICUM SINENSE SUBSP. CHUANXIONG ROOT; MYRRH; OLIVE OIL; PANAX NOTOGINSENG ROOT; RUBIA CORDIFOLIA ROOT; SAFFLOWER; SALVIA MILTIORRHIZA ROOT; SENEGALIA CATECHU WOOD; SPATHOLOBUS SUBERECTUS STEM; TAXILLUS CHINENSIS TOP; WHITE WAX

Drug Facts

Active ingredients
Camphor 11%
Menthol 16%
Methyl salicylate 30%

Purpose
External analgesic
External analgesic
External analgesic

Uses
For the temporary relief of minor aches and pains of muscles and joints due to:
■ simple backache
■ arthritis
■ strains
■ bruises
■ sprains

Warnings
For external use only

Do not use
■ on irritated or damaged skin
■ on wounds

Ask a doctor or pharmacist before use if you have
■ any concerns about using this product

When using this product
■ do not use otherwise than as directed
■ avoid contact with the eyes or mucous membranes
■ do not bandage tightly
■ do not apply heat to the area in the form of heating pads, hot water bottles, or lamps (doing so increases the risk of serious burns)

Stop use and ask a doctor if
■ condition worsens
■ symptoms persist for more than 7 days
■ symptoms clear up and occur again within a few days
■ excessive irritation of the skin develops
■ nausea, vomiting, abdominal discomfort, diarrhea, or skin rash occurs
■ you feel actual pain or experience blistering or burning after application (it is normal to feel a warming or cooling sensation)
■ when using for pain of arthritis:
■ pain persists for more than 10 days
■ redness is present
■ in conditions affecting children under 12 years of age

ADVERSE REACTIONS

Report any unexpected side effectsfrom the use of this product to the FDA MedWatch Program

KEEP OUT OF REACH OF CHILDREN

Keep out of reach of childrento avoid accidental poisoning. If swallowed, get medical help or contact a Poison Control Center right away.

Directions
■ adults and children 3 years of age and older: apply several drops and rub Into the affected area not more than 3 to 4 times daily
■ children under 3 years of age: consult your physician

Other information
■ keep container tightly closed
■ store protected from light at 15 to 30 C (59 To 86 F)

Inactive ingredients
angelica sinensis root, biancaea sappan wood, citrus aurantium fruit, crassostrea gigas shell, cyathula officinalis root, dipsacus asper root, dragon's blood, eucommia ulmoides bark, frankincense, leonurus japonicus flowering top, ligusticum sinense subsp. chuanxiong root, myrrh, olive oil, panax notoginseng root, rubia cordifolia root, safflower, salvia miltiorrhiza root, senegalia catechu wood, spatholobus suberectus stem, taxillus chinensis top and white wax.

Questions or comments? (888) 221-3496M-F 9 am to 5 pm
■ you may also report serious side effects to this phone number

PACKAGE LABEL

NECK AND LUMBAR PAIN RELIEVING BALM

NDC 55614-661-01

EXTERNAL ANALGESIC

CAMPHOR, MENTHOL, and METHYL SALICYLATE

2.82 OZ (80 G)